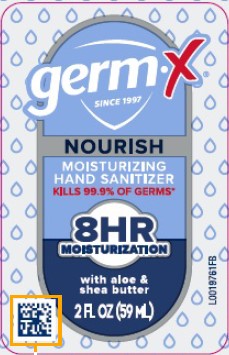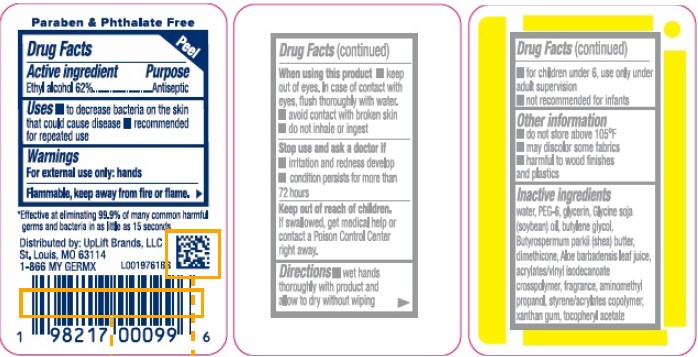 DRUG LABEL: Hand Sanitizer
NDC: 83986-815 | Form: GEL
Manufacturer: UpLift Brands, LLC
Category: otc | Type: HUMAN OTC DRUG LABEL
Date: 20250325

ACTIVE INGREDIENTS: ALCOHOL 62 mL/100 mL
INACTIVE INGREDIENTS: WATER; POLYETHYLENE GLYCOL 300; GLYCERIN; SOYBEAN OIL; BUTYLENE GLYCOL; SHEA BUTTER; DIMETHICONE; ALOE VERA LEAF; ACRYLATES/VINYL ISODECANOATE CROSSPOLYMER (10000 MPA.S NEUTRALIZED AT 0.5%); AMINOMETHYLPROPANOL; STYRENE/ACRYLAMIDE COPOLYMER (500000 MW); XANTHAN GUM; .ALPHA.-TOCOPHEROL ACETATE

Germ-X 815.001/815AC
Moisturizing Hand Sanitizer

Claims

Paraben & Phthalate Free

Active ingredient

Ethyl alcohol 62%

Purpose

Antiseptic

Uses

- to decrease bacteria on the skin that could cause disease
- recommended for repeated use

Warnings

For external use only: hands

Flammable, keep away from fire or flame.

When using this product

- keep out of eyes. In case of contact with eyes, flush thoroughly with water.
- avoid contact with broken skin
- do not inhale or ingest

Stop use and ask a doctor if

- irritation and redness develop
- condition persists for more than 72 hours

Keep out of reach of children

If swallowed, get medical help or contact a Poison Control Center right away.

Directions

- wet hands thoroughly with product and allow to dry without wiping
- for children under 6, use only under adult supervision
- not recommended for infants

Other information

- do not store above 105⁰ F
- may discolor some fabrics
- harmful to wood finishes and plastics

Inactive ingredients

water, PEG-6, glycerin, Glycine soja (soybean) oil, butylene glycol, Butyrospermum parkii (shea) butter, dimethicone, Aloe barbadensis leaf juice, acrylates/vinyl isodecanoate crosspolymer, fragrance, aminomethyl propanol, styrene/acrylates copolymer, xanthan gum, tocopheryl acetate

Adverse reaction

Distributed by: UpLift Brands, LLC

St. Louis, MO 63114

1-866 MY GERMX

Disclaimer

*Effective at eliminating 99.9% of many common harmful germs and bacteria in as little as 15 seconds.

principal panel display

germ-x®

SINCE 1997

NOURISH

MOISTURIZING

HAND SANITIZER

KILLS 99.9% OF GERMS

8HR

MOISTURIZATION

with aloe & shea butter

2 FL OZ (59 mL)